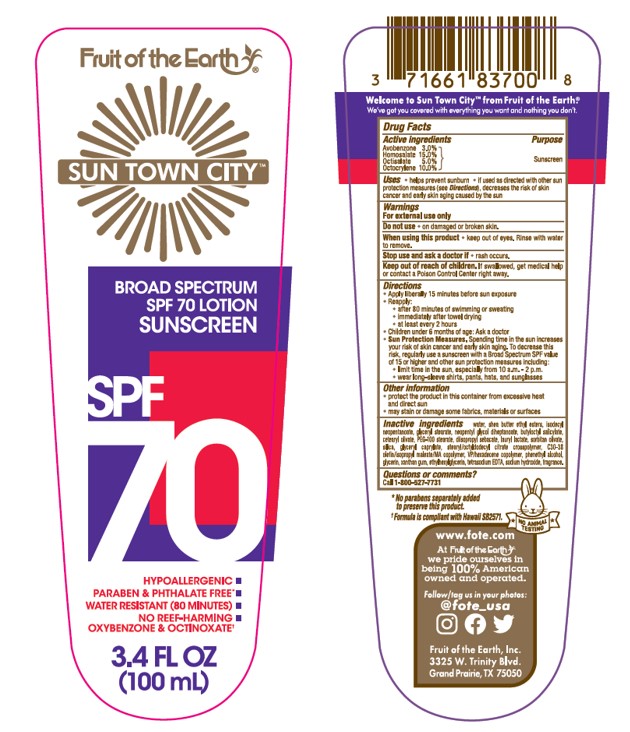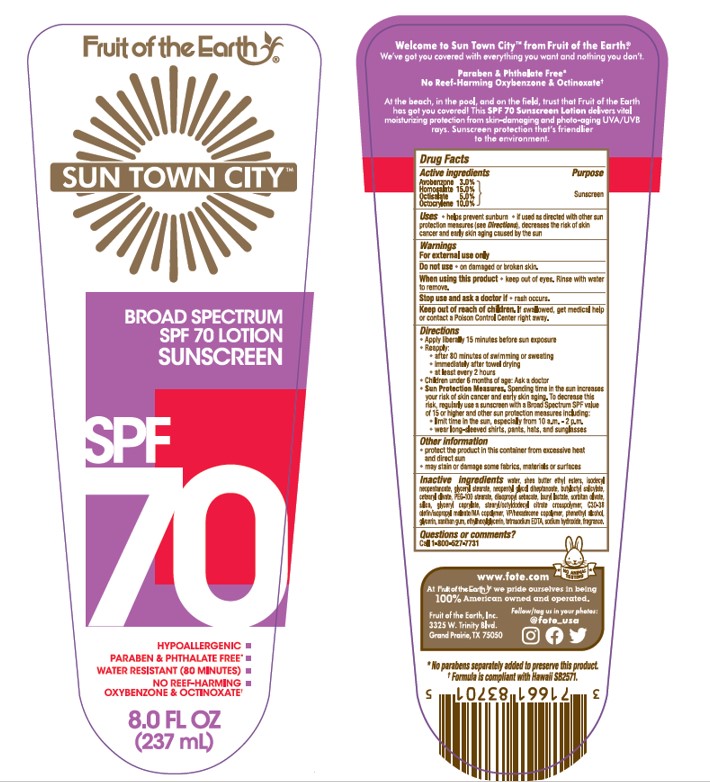 DRUG LABEL: Fruit of the Earth Sun Town City Mineral SPF 70 Sunscreen
NDC: 62217-250 | Form: LOTION
Manufacturer: Fruit Of The Earth, Inc.
Category: otc | Type: HUMAN OTC DRUG LABEL
Date: 20241018

ACTIVE INGREDIENTS: OCTISALATE 50 mg/1 mL; HOMOSALATE 150 mg/1 mL; AVOBENZONE 30 mg/1 mL; OCTOCRYLENE 100 mg/1 mL
INACTIVE INGREDIENTS: ISODECYL NEOPENTANOATE; DIISOPROPYL SEBACATE; LAURYL LACTATE; CETEARYL OLIVATE; XANTHAN GUM; ETHYLHEXYLGLYCERIN; SILICON DIOXIDE; GLYCERYL 1-STEARATE; STEARYL/OCTYLDODECYL CITRATE CROSSPOLYMER; VINYLPYRROLIDONE/HEXADECENE COPOLYMER; WATER; GLYCERIN; SODIUM HYDROXIDE; BUTYLOCTYL SALICYLATE; NEOPENTYL GLYCOL DIHEPTANOATE; EDETATE DISODIUM; PHENYLETHYL ALCOHOL; GLYCERYL CAPRYLATE; SORBITAN OLIVATE; SHEA BUTTER ETHYL ESTERS; PEG-100 STEARATE

Fruit of the Earth Sun Town City Mineral SPF 70 Lotion Sunscreen

Active ingredients

Avobenzone 3.0%

Homosalate 15.0%

Octisalate 5.0%

Octocrylene 10.0%

Purpose

Sunscreen

Uses

• helps prevent sunburn • if used as directed with other sun protection measures (see Directions), decreases the risk of skin cancer and early skin aging caused by the sun

Warnings

For external use only

Do not use

•on damaged or broken skin.

When using this product

• keep out of eyes. Rinse with water to remove.

Stop use and ask a doctor if

• rash occurs.

Keep out of reach of children

If product is swallowed, get medical help or contact a Poison Control Poison Control Center right away.

Directions

• apply liberally 15 minutes before sun exposure

• reapply:

• after 80 minutes of swimming or sweating

• immediately after towel drying

• at least every 2 hours

• children under 6 months of age: Ask a doctor

• Sun Protection Measures. Spending time in the sun increases your risk of skin cancer and early skin aging. To decrease this risk, regularly use a sunscreen with a Broad Spectrum SPF value of 15 or higher and other sun protection measures including:

• limit time in the sun, especially from 10 a.m. - 2 p.m.

• wear long-sleeved shirts, pants, hats, and sunglasses

Other information

• protect the product in this container from excessive heat and direct sun

• may stain or damage some fabrics, materials or surfaces

Inactive ingredients

Water, Shea Butter Ethyl Esters, Isodecyl Neopentanoate, Glyceryl Stearate, Neopentyl Glycol Diheptanoate, Butyloctyl Salicylate, Cetearyl Olivate, PEG-100 Stearate, Diisopropyl Sebacate, Lauryl Lactate, Sorbitan Olivate, Silica, Glyceryl Caprylate, Stearyl/Octyldodecyl Citrate Crosspolymer, C30-38 Olefin/Isopropyl Maleate/MA Copolymer, VP/Hexadecene Copolymer, Phenethyl Alcohol, Glycerin, Xanthan Gum, Ethylhexylglycerin, Tetrasodium EDTA, Sodium Hydroxide, Fragrance.